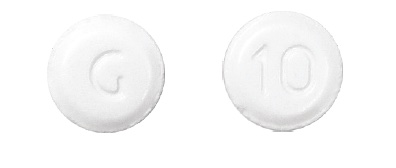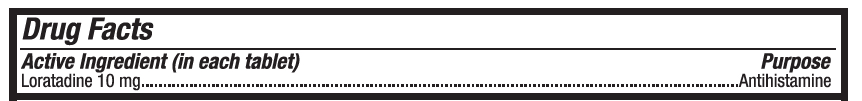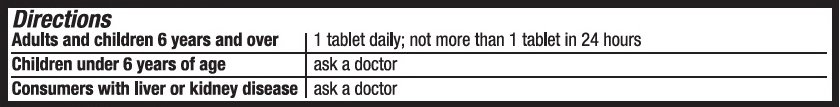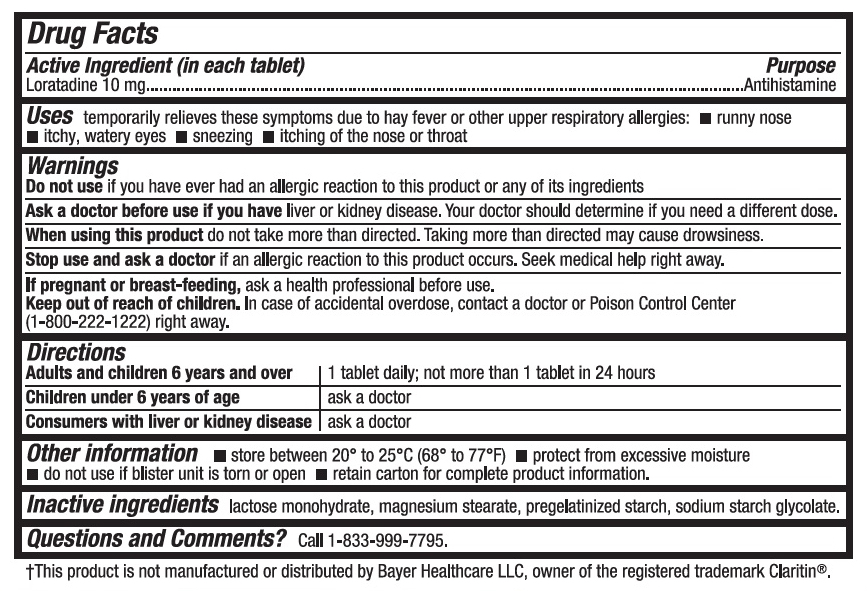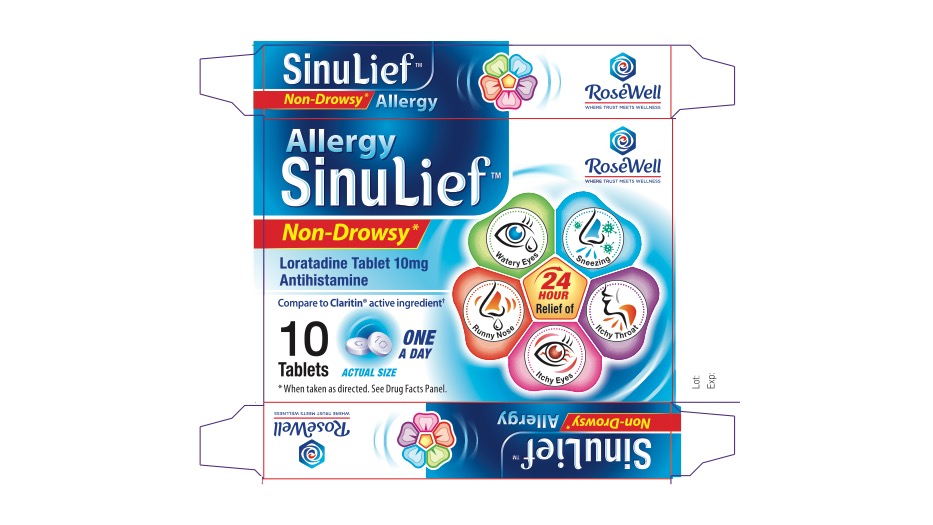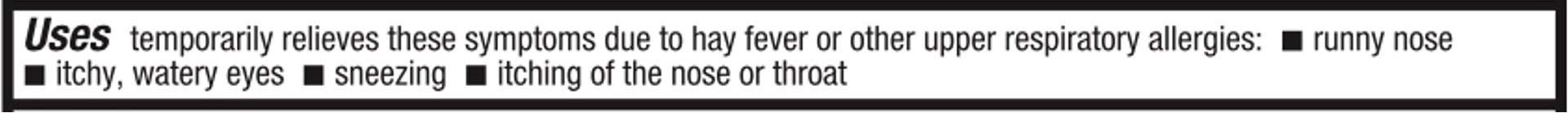 DRUG LABEL: SinuLief
NDC: 85510-101 | Form: TABLET
Manufacturer: RoseWell Pharmaceuticals LLC
Category: otc | Type: HUMAN OTC DRUG LABEL
Date: 20251006

ACTIVE INGREDIENTS: LORATADINE 10 mg/1 1
INACTIVE INGREDIENTS: LACTOSE MONOHYDRATE; MAGNESIUM STEARATE; SODIUM STARCH GLYCOLATE TYPE A CORN

Active Ingredient (in each tablet)

Loratadine 10 mg.....................................................................................................Antihistamine

WARNINGS

Do not use

if you have ever had an allergic reaction to this product or any of its ingredients

Ask a doctor before use if you have

liver or kidney disease. Your doctor should determine if you need a different dose.

When using this product

do not take more than directed. Taking more than directed may cause drowsiness.

Stop use and ask a doctor

if an allergic reaction to this product occurs. Seek medical help right away.

I pregnant or breast-feeding

ask a health professional before use.

Keep out of reach of children

In case of accidental overdose, contact a doctor or Poison Control Center (1-800-222-1222) right away.

WHEN USING

Adults and children 6 years and older 1 tablet daily; not more than 1 tablet in 24 hours

Children under 6 years of age ask a doctor

Consumers with liver or kidney disease ask a doctor

Other information

- store between 20° to 25°C (68°-77° F)
- protect from excessive moisture
- do not use if blister unit is torn or open
- retain carton for complete product information.

Innactive ingredients

lactose monohydrate, magnesium stearate, pregelatinized starch, sodium starch glycolate.

Questions and Comments?

Call 1-833-999-7795

PURPOSE

Temporarily relieves these symptoms due to hay fever or other upper respiratory allergies:

- runny nose
- itchy, watery eyes
- sneezing
- itching of the nose or throat

INDICATIONS AND USAGE

Temporarily relieves these symptoms due to hay fever or other upper respiratory allergies:

- runny nose
- itchy, watery eyes
- sneezing
- itching of the nose or throat